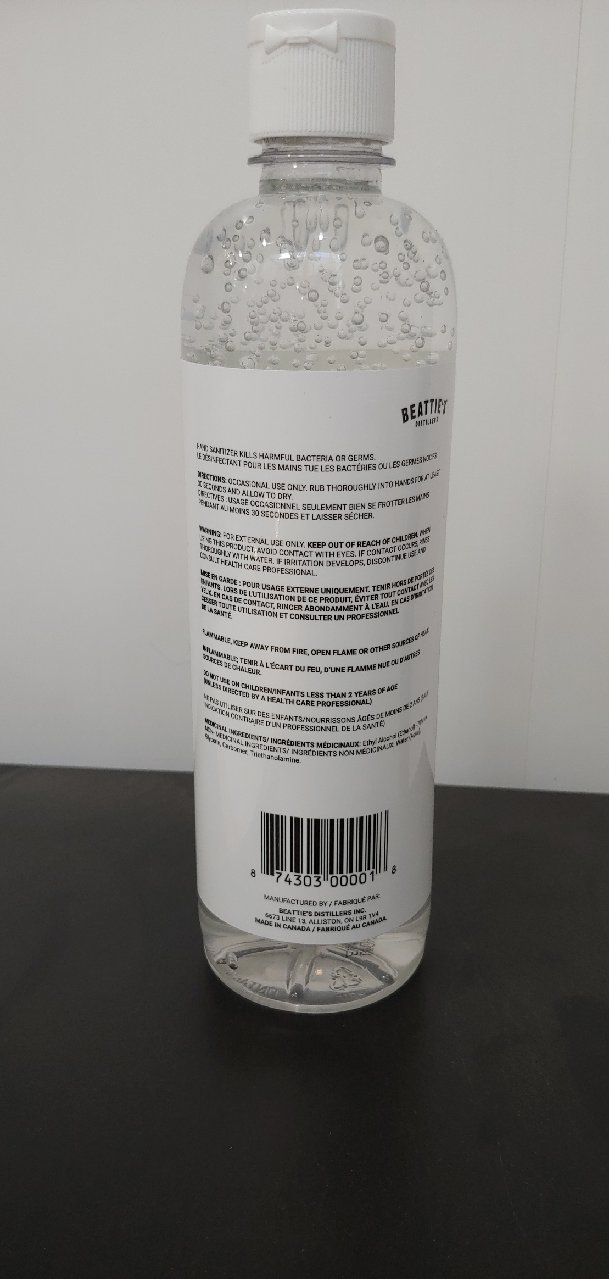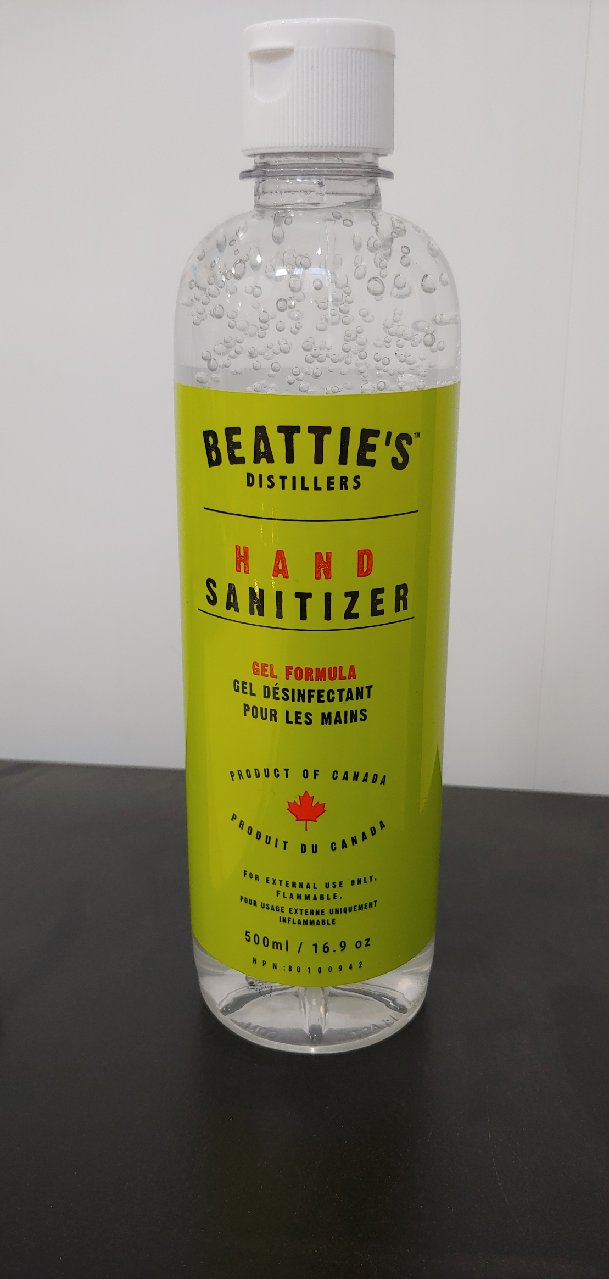 DRUG LABEL: Hand Sanitizer
NDC: 77427-6311 | Form: GEL
Manufacturer: Beattie's Distillers Inc.
Category: otc | Type: HUMAN OTC DRUG LABEL
Date: 20220124

ACTIVE INGREDIENTS: ALCOHOL 70 mL/100 mL
INACTIVE INGREDIENTS: WATER; CARBOMER 940 0.5 mL/100 mL; GLYCERIN 1.45 mL/100 mL; HYDROGEN PEROXIDE 0.125 mL/100 mL

This is a hand sanitizer manufactured according to the Temporary Policy for Preparation of Certain Alcohol-Based Hand Sanitizer Products During the Public Health Emergency (CoViD-19); Guidance for Industry.

The hand sanitizer is manufactured using only the following United States Pharmacopoeia (USP) grade ingredients in the preparation of the product (percentage in final product formulation) consistent with World Health Organization (WHO) recommendations:

1. Alcohol (ethanol) (USP or Food Chemical Codex (FCC) grade) (70%, volume/volume (v/v)) in an aqueous solution denatured according to Alcohol and Tobacco Tax and Trade Bureau regulations in 27 CFR part 20.
2. Glycerol (1.45% v/v).
3. Hydrogen peroxide (0.125% v/v).
4. Carbomer 940 (0.5% v/v)
5. Sterile distilled water or boiled cold water.

The firm does not add other active or inactive ingredients. Different or additional ingredients may impact the quality and potency of the product.

Active Ingredient(s)

Alcohol 70% v/v. Purpose: Antiseptic

Purpose

Antiseptic, Hand Sanitizer

Use

Hand Sanitizer kills harmful bacteria or germs.

Warnings

For external use only. Keep out of reach of children. Flammable. Keep away from fire, open flame or other sources of heat.

Do not use

- in children less than 2 years of age

When using this product avoid contact with eyes. If contact occurs, rinse thoroughly with water.
If irritation develops, discontinue use and consult a health care professional.
Keep out of reach of children.

Stop use and ask a doctor if irritation occurs.

Keep out of reach of children. If swallowed, get medical help or contact a Poison Control Center right away.

Directions

- Occasional use only.
- Rub thoroughly into hands for 30 seconds and allow to dry.

Other information

- Store between 15-30C (59-86F)
- Avoid freezing and excessive heat above 40C (104F)

Inactive ingredients

glycerin, hydrogen peroxide, purified water, carbomer 940

Package Label - Principal Display Panel

500 mL NDC: 77427-6311-5